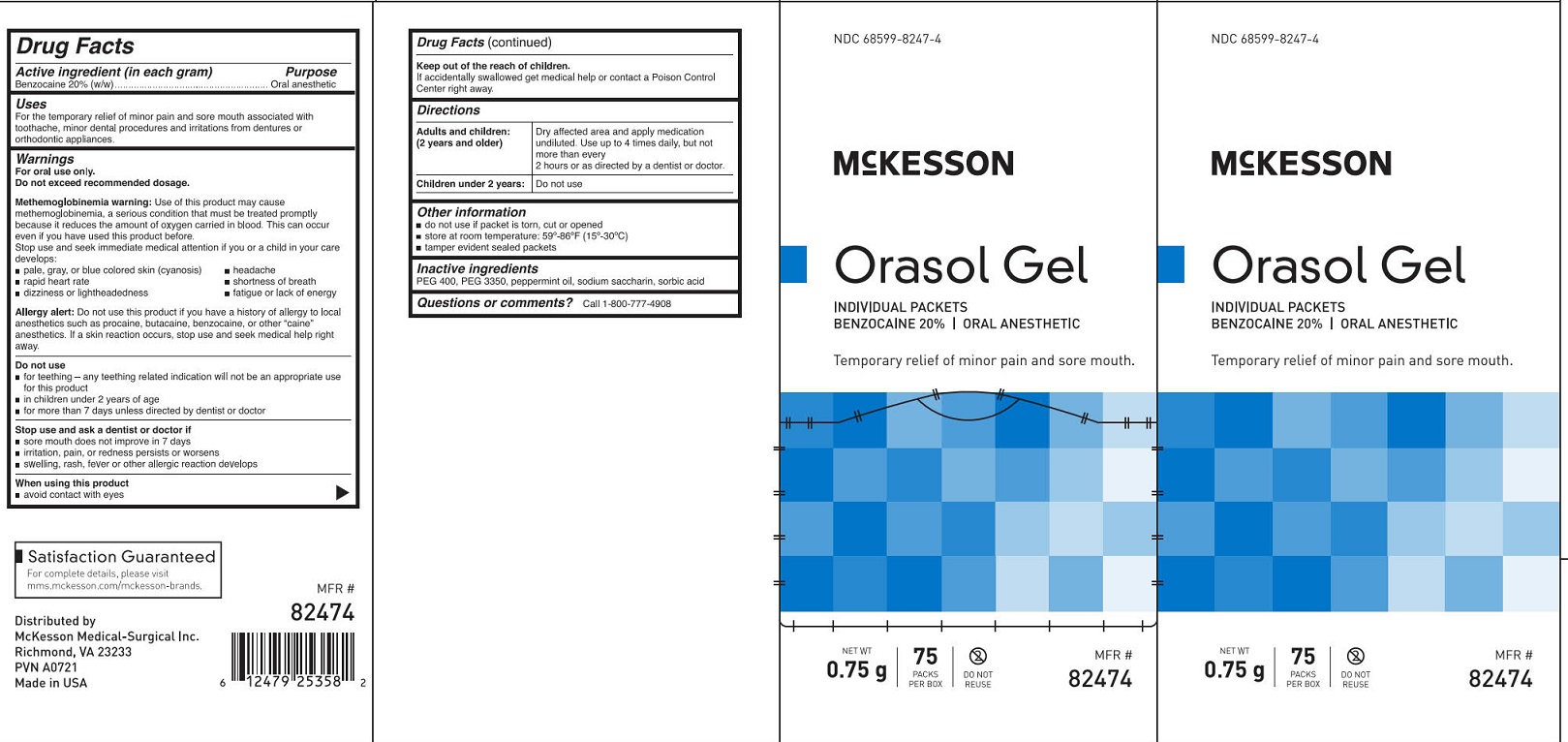 DRUG LABEL: McKesson Orasol Gel
NDC: 68599-8247 | Form: GEL
Manufacturer: McKesson Medical-Surgical
Category: otc | Type: HUMAN OTC DRUG LABEL
Date: 20250909

ACTIVE INGREDIENTS: BENZOCAINE 200 mg/1 g
INACTIVE INGREDIENTS: POLYETHYLENE GLYCOL 3350; POLYETHYLENE GLYCOL 400; PEPPERMINT OIL; SACCHARIN SODIUM; SORBIC ACID

McKesson Orasol Gel

Drug Facts

Active ingredient

Benzocaine 20% (w/w)

Purpose

Oral anesthetic

Uses

For the temporary relief of minor pain and sore mouth associated with toothache, minor dental procedures and irritations from dentures or orthodontic appliances.

Warnings

For oral use only.

Do not exceed recommended dosage.

Methemoglobinemia warning:

Use of this product may cause methemoglobinemia, a serious condition that must be treated promptly because it reduces the amount of oxygen carried in the blood. This can occur even if you have used this product before.

Stop use and seek medical attention if you or a child in your care develops:

- pale, gray or blue colored skin (cyanosis)
- rapid heart rate
- dizziness or lightheadedness
- headache
- shortness of breath
- fatigue or lack of energy

Allergy alert:

Do not use this product if you have a history of allergy to local anesthetics, such as procaine, butacaine, benzocaine, or other “caine” anesthetics. If a skin reaction occurs, stop use and seek medical help right away.

Do not use

- for teething - any teething related indication will not be ab appropriate use of this product
- in children under 2 years of age
- for more than 7 days unless directed by a doctor

Stop use and ask a dentist or doctor if

- sore mouth does not improve in 7 days
- irritation, pain, or redness persists or worsens
- swelling, rash, fever or other allergic reaction develops

When using this product

- avoid contact with eyes

Keep out of reach of children.

If accidentally swallowed get medical help or contact a Poison Control Center right away.

Directions

Adults and children (2 years and older):

Dry affected area and apply medication undiluted. Use up to 4 times daily, but not more than every two hours, or as directed by a dentist or doctor.

Children under 2 years:

Do not use

Other information

- do not use if packet is torn, cut or opened
- store at room temperature: 59° to 86°F (15° to 30°C)
- tamper evident sealed packets

Inactive ingredients

PEG 400, PEG 3350, peppermint oil, sodium saccharin, sorbic acid

Questions or comments? Call 1-800-777-4908

PACKAGE LABEL

NDC 68599-8247-4

McKesson

Orasol Gel

Individual Packets

Benzocaine 20% | Oral Anesthetic

Temporary relief of minor pain and sore mouth.

NET WT 0.75 g

75 Packs Per Box

Do Not Reuse

MFR # 82474